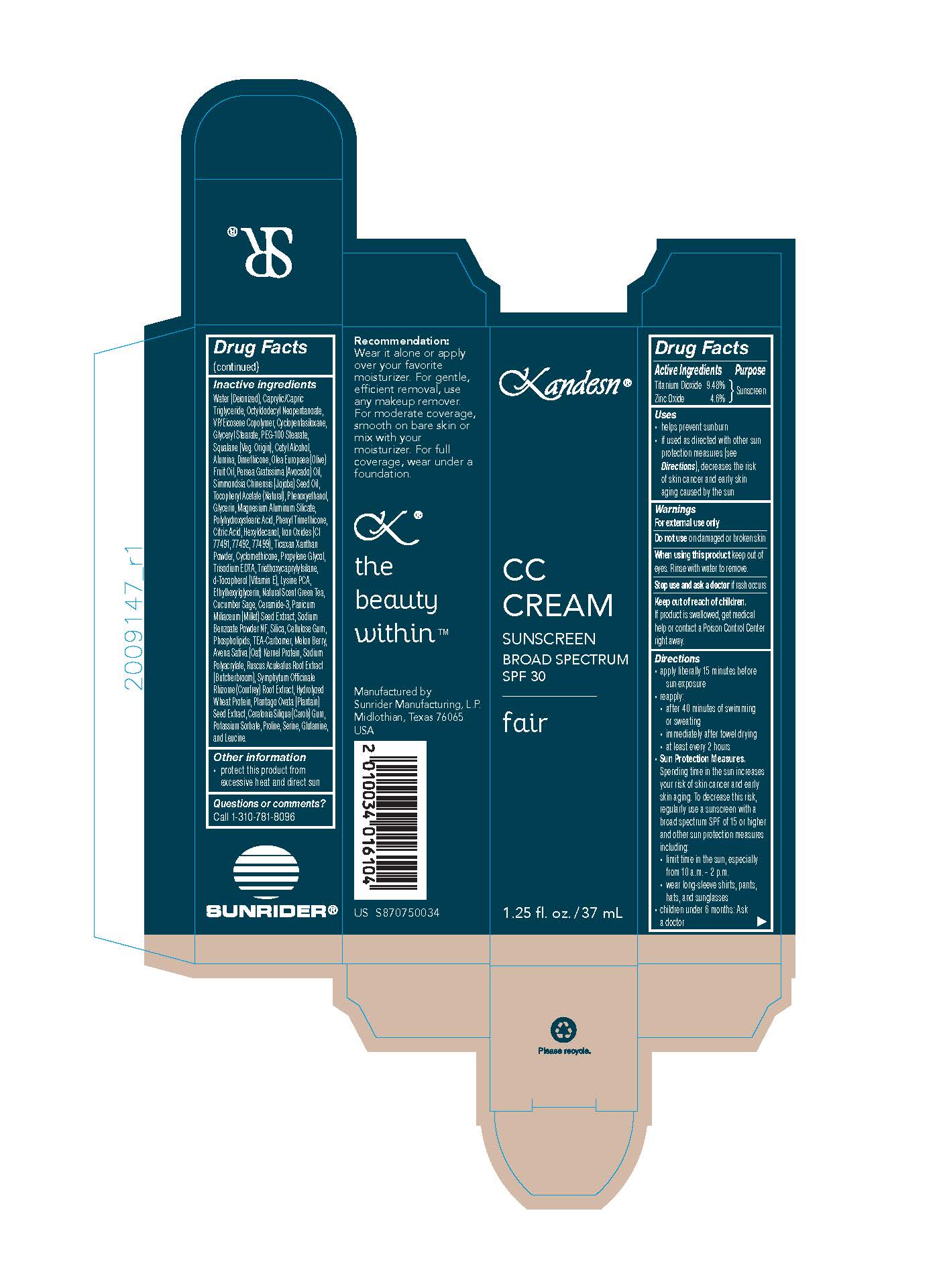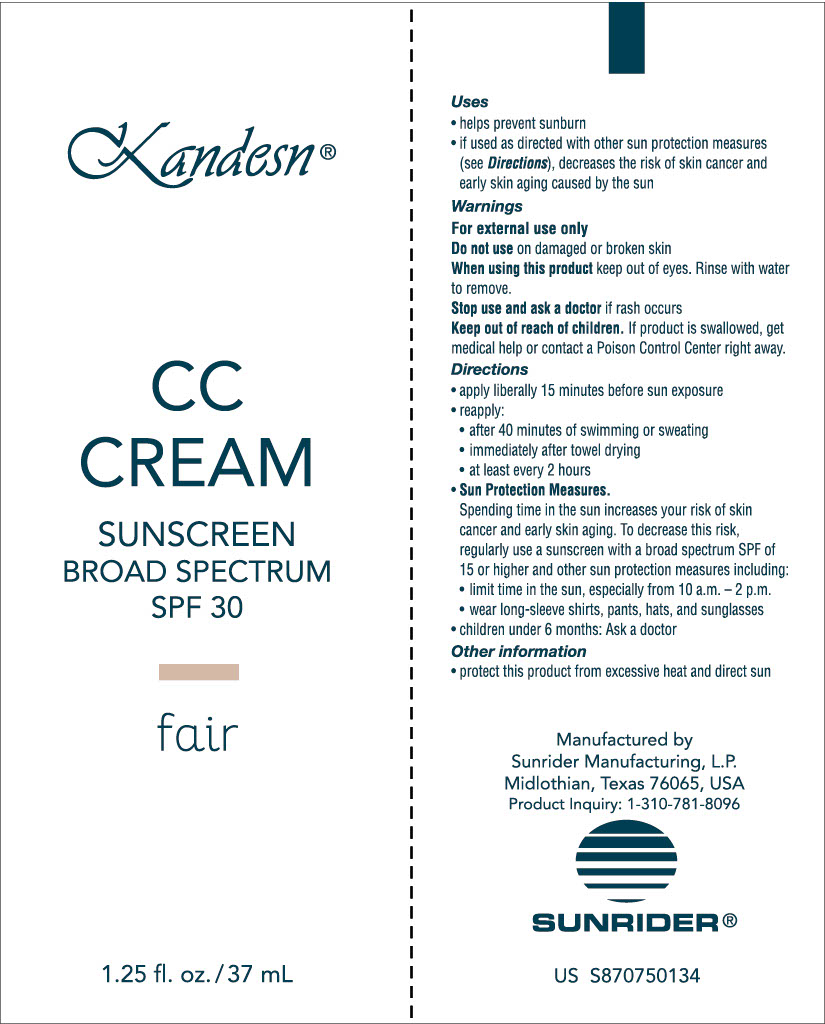 DRUG LABEL: Kandesn CC Cream
NDC: 62191-118 | Form: CREAM
Manufacturer: Sunrider Manufacturing L.P.
Category: otc | Type: HUMAN OTC DRUG LABEL
Date: 20251230

ACTIVE INGREDIENTS: TITANIUM DIOXIDE 114 mg/1 g; ZINC OXIDE 55 mg/1 g
INACTIVE INGREDIENTS: FERRIC OXIDE RED; FERROSOFERRIC OXIDE; OLEA EUROPAEA (OLIVE) FRUIT OIL; PERSEA GRATISSIMA (AVOCADO) OIL; SIMMONDSIA CHINENSIS (JOJOBA) SEED OIL; .ALPHA.-TOCOPHEROL ACETATE; PHENOXYETHANOL; GLYCERIN; MAGNESIUM ALUMINUM SILICATE; POLYHYDROXYSTEARIC ACID (2300 MW); PHENYL TRIMETHICONE; CITRIC ACID; HEXYLDECANOL; FERRIC OXIDE YELLOW; XANTHAN GUM; CYCLOMETHICONE; PROPYLENE GLYCOL; TRISODIUM EDTA; TRIETHOXYCAPRYLYLSILANE; .DELTA.-TOCOPHEROL; LYSINE PCA; ETHYLHEXYLGLYCERIN; GREEN TEA LEAF; SAGE; CERAMIDE 3; MILLET; SODIUM BENZOATE; HYDRATED SILICA; CELLULOSE GUM; EGG PHOSPHOLIPIDS; CARBOMER; MELON; OATMEAL; SODIUM POLYACRYLATE (2500000 MW); RUSCUS ACULEATUS ROOT; COMFREY ROOT; HYDROLYZED WHEAT PROTEIN (ENZYMATIC, 3000 MW); PLANTAGO OVATA SEED; CAROB; POTASSIUM SORBATE; PROLINE; SERINE; GLUTAMINE; LEUCINE; WATER; CAPRYLIC/CAPRIC TRIGLYCERIDE; OCTYLDODECYL NEOPENTANOATE; VINYLPYRROLIDONE/EICOSENE COPOLYMER; CYCLOPENTASILOXANE; GLYCERYL STEARATE; PEG-100 STEARATE; SQUALANE; CETYL ALCOHOL; DIMETHICONE; ALUMINA

Kandesn CC Cream Fair

USES:

- helps prevent sunburn
- if used as directed with other sun protection measures (see Directions), decreased the risk of skin cancer and early skin aging caused by the sun.

DIRECTIONS:

- apply liberally 15 minutes before sun exposure
- Reapply:
- after 40 minutes of swimming or sweating
- immediately after towel drying
- at least every 2 hours
- Sun Protection Measures. Spending time in the sun increases your risk of skin cancer and early skin aging. To decrease this risk, regularly use a sunscreen with a broad spectrum SPF of 15 or higher and other sun protection measures including:
  - limit time in the sun, expecially from 10 a.m. - 2 p.m.
  - wear long-sleeve shirts, pants, hats, and sunglasses
- Children under 6 months: Ask a doctor

ACTIVE INGREDIENTS:

Titanium Dioxide 9.48%
Zinc Oxide 4.6%

INACTIVE INGREDIENT

OTHER INGREDIENTS:

Water (Deionized)
Caprylic/CapricTriglyceride,

Octyldodecyl Neopentanoate,

VP/Eicosene Copolymer,

Cyclopentasiloxane,
Glyceryl Stearate,
PEG-100 Stearate,

Squalane (Veg. Origin),

Cetyl Alcohol,
Alumina,

Dimethicone,
Olea Europaea (Olive) Fruit Oil,

Persea Gratissima (Avocado) Oil,

Simmondsia Chinensis (Jojoba) Seed Oil,

Tocopheryl Acetate (Natural),

Phenoxyethanol,

Glycerin,

Magnesium Aluminum Silicate,

Phenyl Trimethicone,

Citric Acid,

Hexyldecanol,

Iron Oxides (CI 77491, 77492, 77499),

Ticaxan Xanthan Powder,

Cyclomethicone,

Propylene Glycol,

Trisodium EDTA,

Triethoxycaprylylsilane,

d-Tocopherol (Vitamin E),

Lysine PCA,

Ethylhexylglycerin,

Natural Scent Green Tea,

Cucumber Sage,

Ceramide-3,

Panicum Miliaceum (Millet) Seed Extract,

Sodium Benzoate Powder NF,

Silica,

Cellulose Gum,

Phospholipids,

TEA-Carbomer,

Melon Berry,

Avena Sativa (Oat) Kernel Protein,

Sodium Polyacrylate,

Ruscus Aculeatus Root Extract (Butcherbroom),

Symphytum Officinale Rhizome (Comfrey) Root Extract,

Hydrolyzed Wheat Protein,

Plantago Ovata (Plantain) Seed Extract,

Ceratonia Siliqua (Carob) Gum,

Potassium Sorbate,

Proline,

Serine,

Glutamine,

Leucine,

Fragrances

WARNINGS:

FOR EXTERNAL USE ONLY

Do not use on damaged or broken skin

When using this product keep oout of eyes. Rinse with water to remove.

Stop use and ask a doctor if rash occurs.

Keep out of reach of children.

If product is swallowed, get medical help or contact a Poison Control Center right away.

KEEP OUT OF REACH OF CHILDREN. If product is swallowed, get medical help or contact a Poison Control Center right away.

Packaging

Box Tube